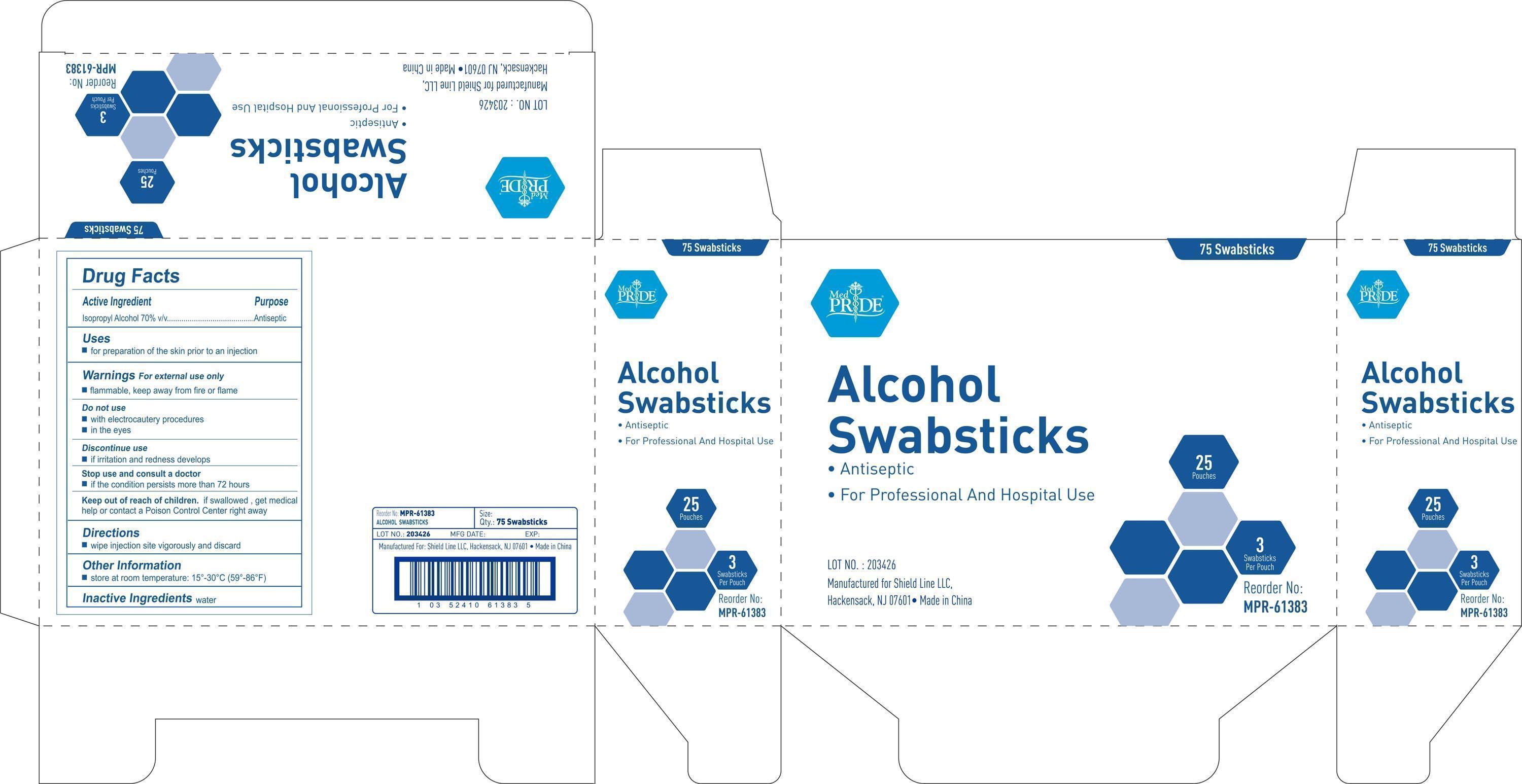 DRUG LABEL: MedPride
NDC: 52410-6138 | Form: SWAB
Manufacturer: Shield Line LLC
Category: otc | Type: HUMAN OTC DRUG LABEL
Date: 20140505

ACTIVE INGREDIENTS: ISOPROPYL ALCOHOL 0.7 mL/1 1
INACTIVE INGREDIENTS: WATER

Drug Facts

Active Ingredient

Isopropyl Alcohol 70% v/v

Purpose

Antiseptic

Uses

■ for preparation of skin prior to injection

Warnings

For external use only
■ flammable, keep away from fire or flame

Do not use

■ with electrocautery procedures

■ in the eyes

Discontinue use

■ if irritation and redness develops

Stop use and ask a doctor if

■ if condition persist for more than 72 hours consult a doctor.

Keep out of reach of children

If swallowed contact a doctor or Poison Control Center right away.

Directions

■wipe injection site vigorously and discard

Other Information

■ store at room temperature:15-30C (59-86F)

Inactive Ingredient

water